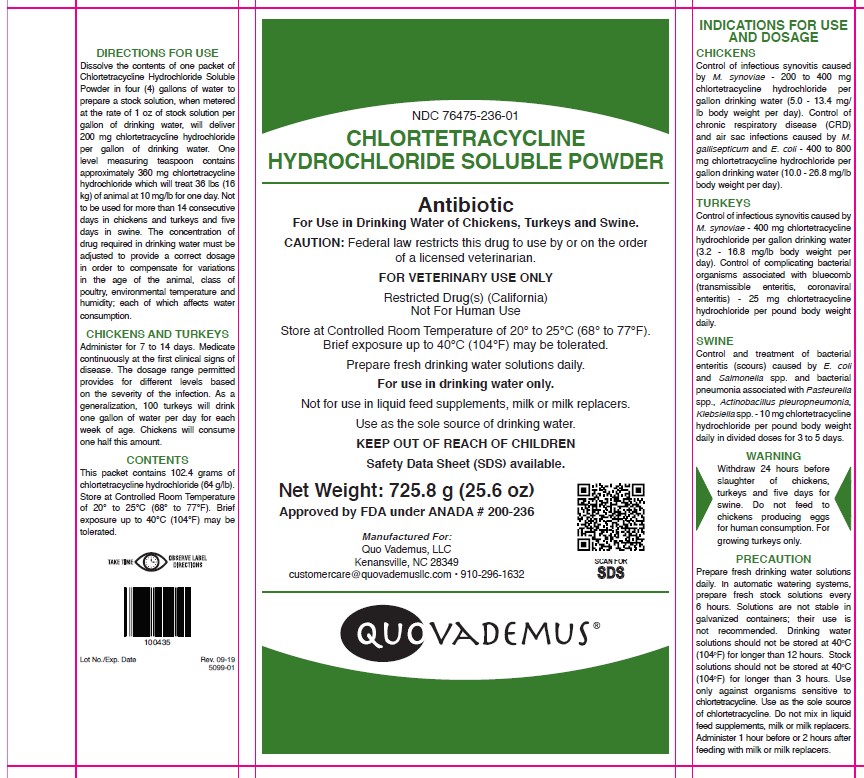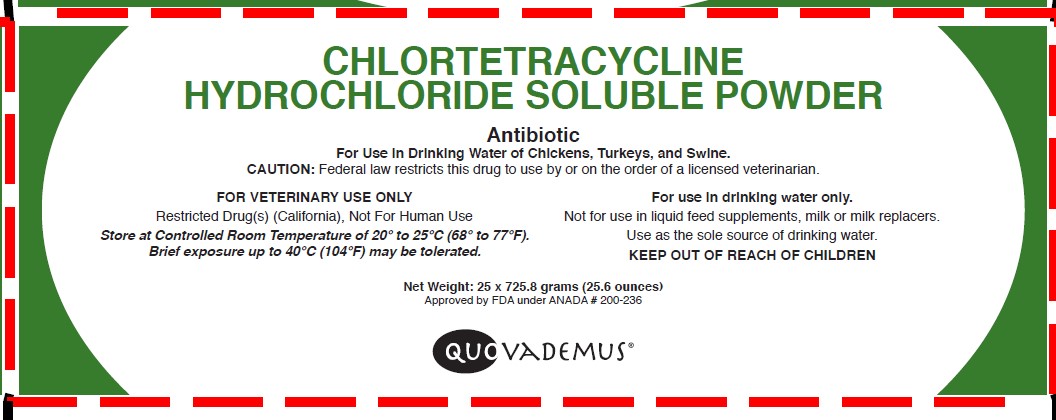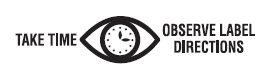 DRUG LABEL: CHLORTETRACYCLINE HYDROCHLORIDE
NDC: 76475-236 | Form: POWDER, FOR SOLUTION
Manufacturer: Quo Vademus
Category: animal | Type: PRESCRIPTION ANIMAL DRUG LABEL
Date: 20231108

ACTIVE INGREDIENTS: CHLORTETRACYCLINE HYDROCHLORIDE 64 g/0.45 kg

NDC 76475-236-01

CHLORTETRACYCLINE HYDROCHLORIDE SOLUBLE POWDER

Antibiotic

For Use in Drinking Water of Chickens, Turkeys and Swine.

CAUTION: Federal law restricts this drug to use by or on the order of a licensed veterinarian.

FOR VETERINARY USE ONLY

Restricted Drug(s) (California) Not for Human Use

Store at Controlled Room Temperature of 20° to 25°C (68° to 77°F). Brief exposure up to 40°C (104°F) may be tolerated.

Prepared fresh drinking water solutions daily.

For use in drinking water only.

Not for use in liquid feed supplements, milk or milk replacers.

Use as the sole source of drinking water.

KEEP OUT OF REACH OF CHILDREN

Safety Data Sheet (SDS) available.

Net Wt 725.8 g (25.6 oz)

Approved by FDA under ANADA # 200-236

Manufactured For:

Quo Vademus, LLC
Kenansville, NC 28349
customercare@quovademusllc.com • 910-296-1632

INDICATIONS FOR USE AND DOSAGE

CHICKENS

Control of infectious synovitis caused by M. synoviae - 200 to 400 mg chlortetracycline hydrochloride per gallon drinking water (5.0 - 13.4 mg/lb body weight per day). Control of chronic respiratory disease (CRD) and air sac infections caused by M. gallisepticum and E. coli - 400 to 800 mg chlortetracycline hydrochloride per gallon drinking water (10.0 - 26.8 mg/lb body weight per day).

TURKEYS

Control of infectious synovitis caused by M. synoviae - 400 mg chlortetracycline hydrochloride per gallon drinking water (3.2 - 16.8 mg/lb body weight per day). Control of complicating bacterial organisms associated with bluecomb (transmissible enteritis, coronaviral enteritis) - 25 mg chlortetracycline hydrochloride per pound body weight daily.

SWINE

Control and treatment of bacterial enteritis (scours) caused by E. coli and Salmonella spp. and bacterial pneumonia associated with Pasteurella spp., Actinobacillus pleuropneumonia, Klebsiella spp. - 10 mg chlortetracycline hydrochloride per pound body weight daily in divided doses for 3 to 5 days.

WARNING

Withdraw 24 hours before slaughter of chickens, turkeys and five days for swine. Do not feed to chickens producing eggs for human consumption. For growing turkeys only.

PRECAUTIONS

Prepare fresh drinking water solutions daily. In automatic watering systems, prepare fresh stock solutions every 6 hours. Solutions are not stable in galvanized containers; their use is not recommended. Drinking water solutions should not be stored at 40°C (104°F) for longer than 12 hours. Stock solutions should not be stored at 40°C (104°F) for longer than 3 hours. Use only against organisms sensitive to chlortetracycline. Use as the sole source of chlortetracycline. Do not mix in liquid feed supplements, milk or milk replacers. Administer 1 hour before or 2 hours after feeding with milk or milk replacers.

DIRECTIONS FOR USE

Dissolve the contents of one packet of Chlortetracycline Hydrochloride Soluble Powder in four (4) gallons of water to prepare a stock solution, when metered at the rate of 1 oz of stock solution per gallon of drinking water, will deliver 200 mg chlortetracycline hydrochloride per gallon of drinking water. One level measuring teaspoon contains approximately 360 mg chlortetracycline hydrochloride which will treat 36 lbs (16 kg) of animal at 10 mg/lb for one day. Not to be used for more than 14 consecutive days in chickens and turkeys and five days in swine. The concentration of drug required in drinking water must be adjusted to provide a correct dosage in order to compensate for variations in the age of the animal, class of poultry, environmental temperature and humidity; each of which affects water consumption.

CHICKENS AND TURKEYS

Administer for 7 to 14 days. Medicate continuously at the first clinical signs of disease. The dosage range permitted provides for different levels based on the severity of the infection. As a generalization, 100 turkeys will drink one gallon of water per day for each week of age. Chickens will consume one half this amount.

CONTENTS

This packet contains 102.4 grams of chlortetracycline hydrochloride (64 g/lb). Store at Controlled Room Temperature of 20° to 25°C (68° to 77°F). Brief exposure up to 40°C (104°F) may be tolerated.

PRINCIPAL DISPLAY PANEL - 25.6 Ounce Packet

NDC 76475-236-01

CHLORTETRACYCLINE HYDROCHLORIDE SOLUBLE POWDER

Antibiotic

For Use in Drinking Water of Chickens, Turkeys and Swine.

CAUTION: Federal law restricts this drug to use by or on the order of a licensed veterinarian.

FOR VETERINARY USE ONLY

Restricted Drug(s) (California) Not for Human Use

Store at Controlled Room Temperature of 20° to 25°C (68° to 77°F). Brief exposure up to 40°C (104°F) may be tolerated.

Prepared fresh drinking water solutions daily.

For use in drinking water only.

Not for use in liquid feed supplements, milk or milk replacers.

Use as the sole source of drinking water.

KEEP OUT OF REACH OF CHILDREN

Safety Data Sheet (SDS) available.

[QR Code]

Scan for SDS

Net Weight: 725.8 g (25.6 oz)

Approved by FDA under ANADA # 200-236

Manufactured For:

Quo Vademus, LLC
Kenansville, NC 28349
customercare@quovademusllc.com • 910-296-1632

Principal Display Panel - 25 pouch carton front display panel

NDC 76475-236-01

CHLORTETRACYCLINE HYDROCHLORIDE SOLUBLE POWDER

Antibiotic

For Use in Drinking Water of Chickens, Turkeys and Swine.

CAUTION: Federal law restricts this drug to use by or on the order of a licensed veterinarian.

FOR VETERINARY USE ONLY

Restricted Drug(s) (California) Not for Human Use

Store at Controlled Room Temperature of 20° to 25°C (68° to 77°F). Brief exposure up to 40°C (104°F) may be tolerated.

For use in drinking water only.

Not for use in liquid feed supplements, milk or milk replacers.

Use as the sole source of drinking water.

KEEP OUT OF REACH OF CHILDREN

LOT NUMBER & EXPIRATION DATE

Net Weight: 25 x 725.8 grams (25.6 ounces)

Approved by FDA under ANADA # 200-236

Before using, read Safety Data Sheet (SDS) for the product.

Manufactured For:

Quo Vademus, LLC
Kenansville, NC 28349
customercare@quovademusllc.com • 910-296-1632